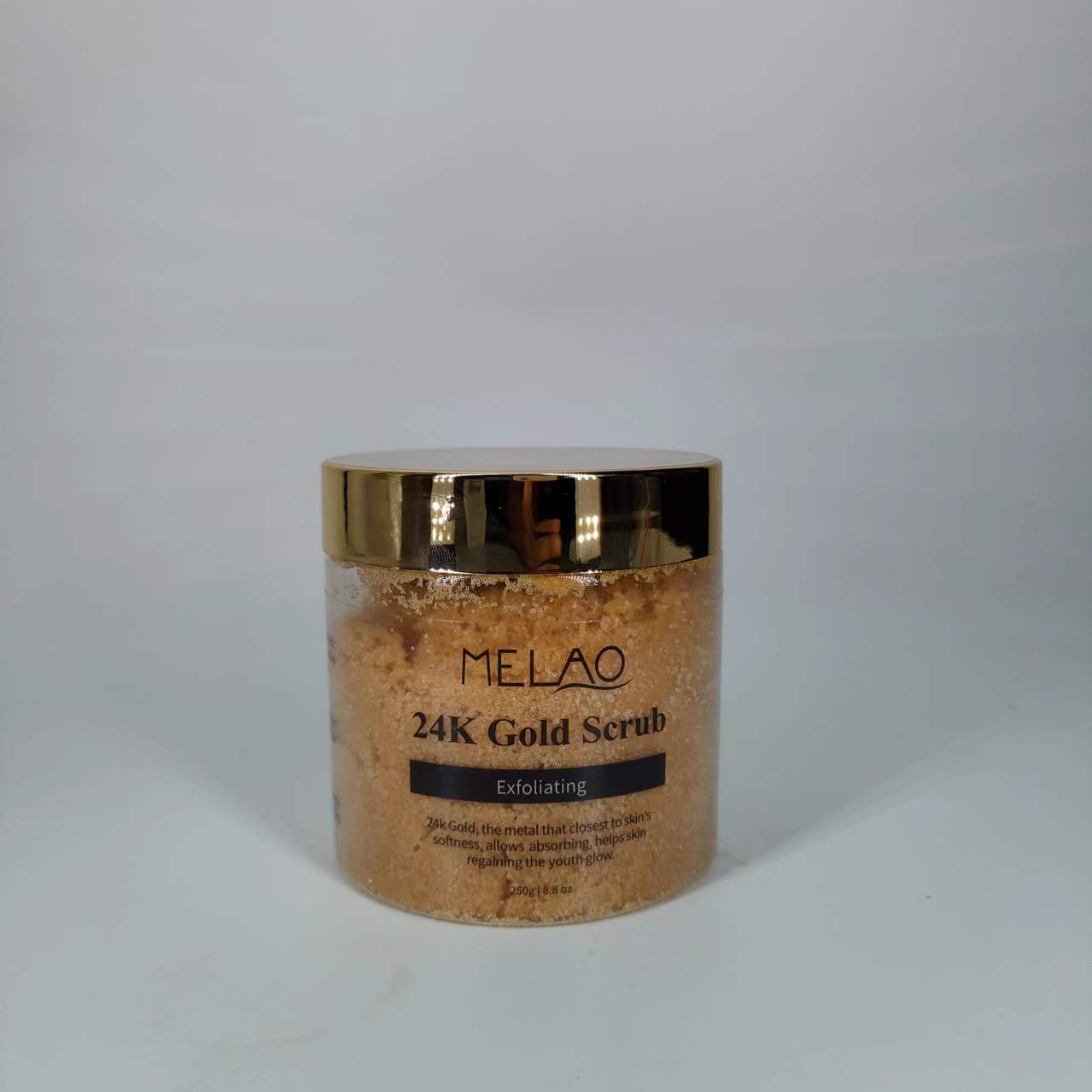 DRUG LABEL: MELAO 24K Gold Scrub
NDC: 74458-002 | Form: GRANULE
Manufacturer: Guangzhou Yilong Cosmetics Co., Ltd
Category: otc | Type: HUMAN OTC DRUG LABEL
Date: 20241108

ACTIVE INGREDIENTS: ALLANTOIN 0.5 g/100 g
INACTIVE INGREDIENTS: GLYCERIN; GOLD; BUTYLENE GLYCOL; XANTHAN GUM; FRUCTOSE; PAEONIA LACTIFLORA ROOT; TOCOPHEROL

INACTIVE INGREDIENT

Fructose

Glycerin

Butylene Glycol

Corn Glutenin Amino Acids

Cereus Grandiflorus (Cactus) Flower Extract

Paeonia Albiflora Root Extract

Tocopherol

Xanthan Gum

Gold

ACTIVE INGREDIENT

Allantoin

PURPOSE

Exfoliation.

INDICATIONS AND USAGE

Once or twice per week, gently massage scrub into damp skin using circular motions. Leave it on for few minutes and then rinse thoroughly with warm water.

Stop use and ask a doctor if rash occurs.

Do not use on damaged or broken skin.

When using this product keep out of eyes. Rinse with water to remove.

Keep out of reach of children. If swallowed, get medical help or contact a Poison Control Center right away.

DOSAGE AND ADMINISTRATION

Once or twice per week, gently massage scrub into damp skin using circular motions. Leave it on for few minutes and then rinse thoroughly with warm water.

WARNINGS

For external use only.